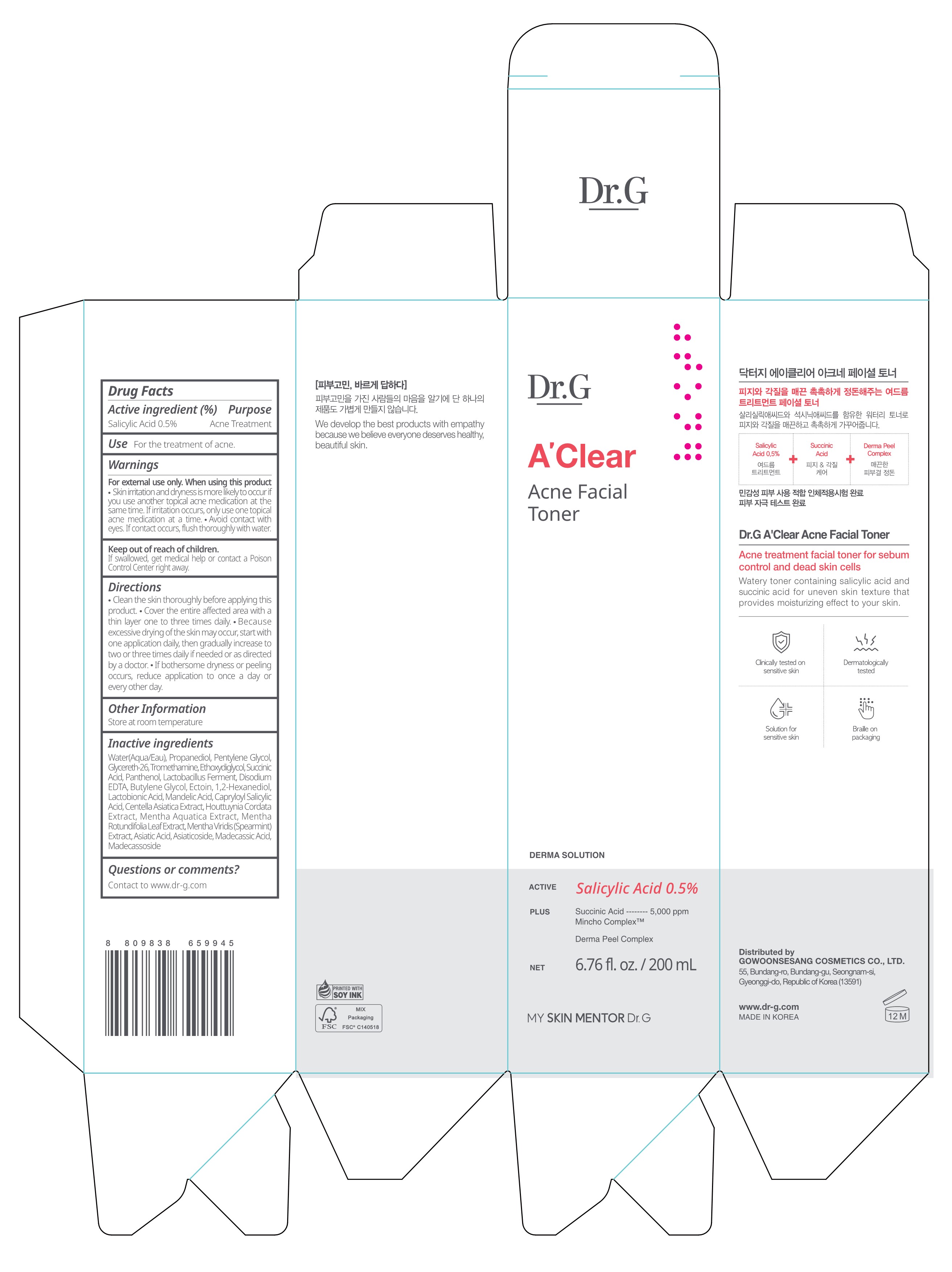 DRUG LABEL: Dr.G A CLEAR ACNE FACIAL TONER
NDC: 51621-411 | Form: LIQUID
Manufacturer: GOWOONSESANG COSMETICS CO., LTD.
Category: otc | Type: HUMAN OTC DRUG LABEL
Date: 20250320

ACTIVE INGREDIENTS: SALICYLIC ACID 0.5 g/100 mL
INACTIVE INGREDIENTS: WATER; PENTYLENE GLYCOL; PROPANEDIOL; GLYCERETH-26; TROMETHAMINE; EDETATE DISODIUM; MENTHA X ROTUNDIFOLIA LEAF; MADECASSIC ACID; MADECASSOSIDE; BUTYLENE GLYCOL; 1,2-HEXANEDIOL; LACTOBIONIC ACID; MENTHA SPICATA; ASIATICOSIDE; PANTHENOL; ETHOXYDIGLYCOL; CAPRYLOYL SALICYLIC ACID; ASIATIC ACID; CENTELLA ASIATICA TRITERPENOIDS; HOUTTUYNIA CORDATA FLOWERING TOP; SUCCINIC ACID; ECTOINE; MANDELIC ACID

Active ingredient

Salicylic Acid 0.5%

Purpose

Acne Treatment

Use

For the treatment of acne.

Warnings

For external use only. When using this product

- Skin irritation and dryness is more likely to occur if you use another topical acne medication at the same time.If irritation occurs, only use one topical acne medication at a time.
- Avoid contact with eyes. If contact occurs, flush thoroughly with water.

Keep out of reach of children.

If swallowed, get medical help or contact a Poison Control Center right away.

Directions

- Clean the skin thoroughly before applying this product.
- Cover the entire affected area with a thin layer one to three times daily.
- Because excessive drying of the skin may occur, start with one application daily, then gradually increase to two or three times daily if needed or as directed by a doctor.
- If bothersome dryness or peeling occurs, reduce application to once a day or every other day.

Other Information

Store at room temperature

Inactive Ingredients

Water(Aqua/Eau), Propanediol, Pentylene Glycol, Glycereth-26, Tromethamine, Ethoxydiglycol, Succinic Acid, Panthenol, Lactobacillus Ferment, Disodium EDTA, Butylene Glycol, Ectoin, 1,2-Hexanediol, LactobionicAcid, MandelicAcid, Capryloyl Salicylic Acid, Centella Asiatica Extract, Houttuynia Cordata Extract, Mentha Aquatica Extract, Mentha Rotundifolia Leaf Extract, Mentha Viridis (Spearmint)
Extract, Asiatic Acid, Asiaticoside, Madecassic Acid, Madecassoside

Questions or comments?

Contact to www.dr-g.com